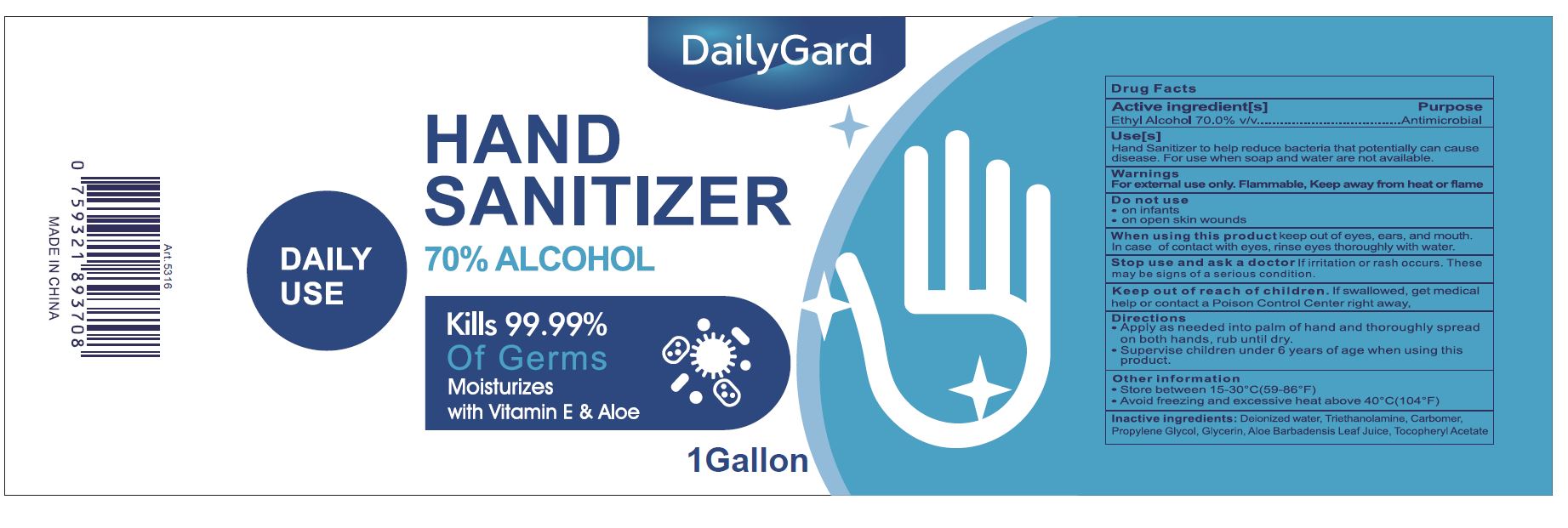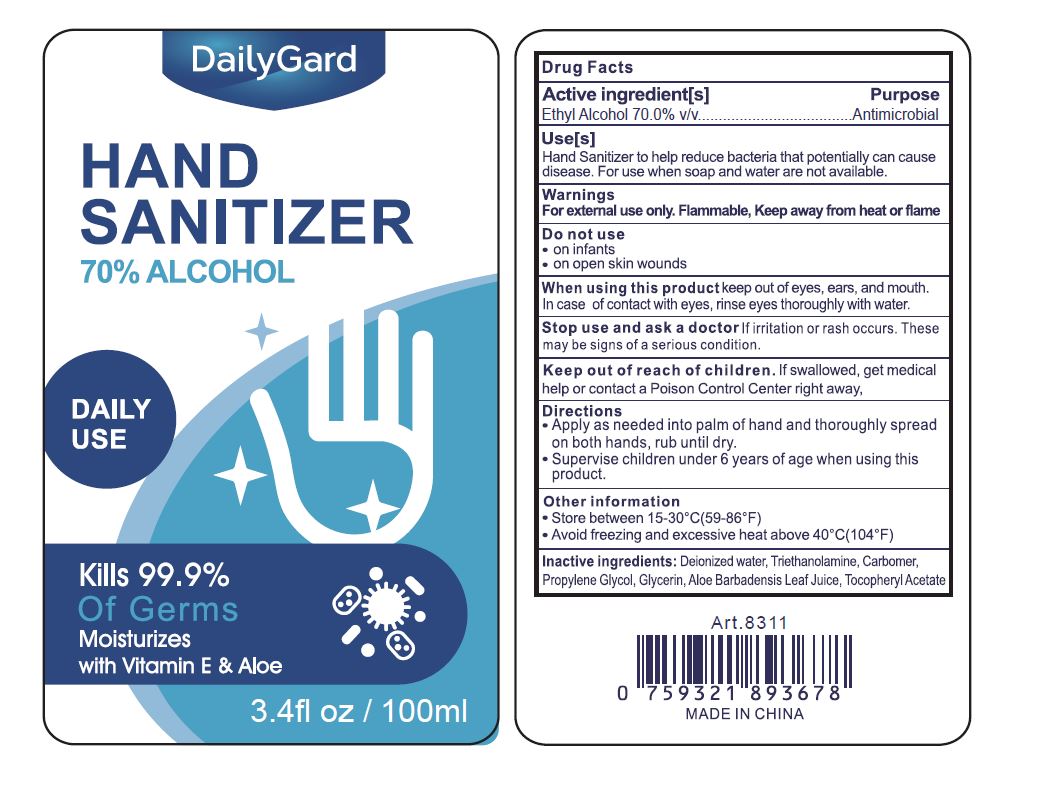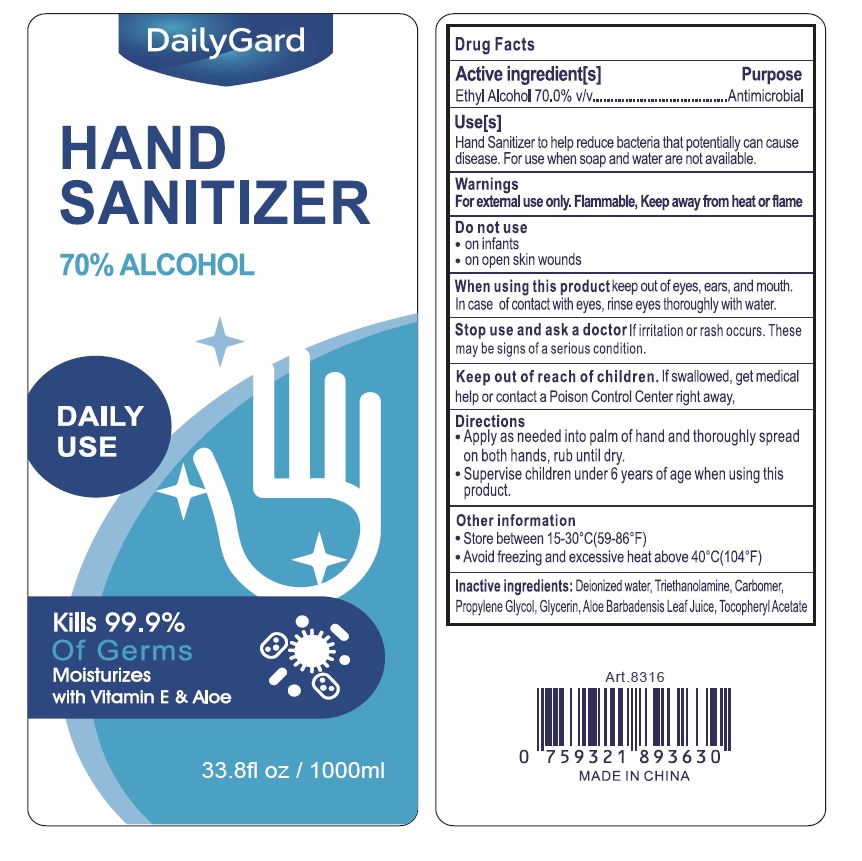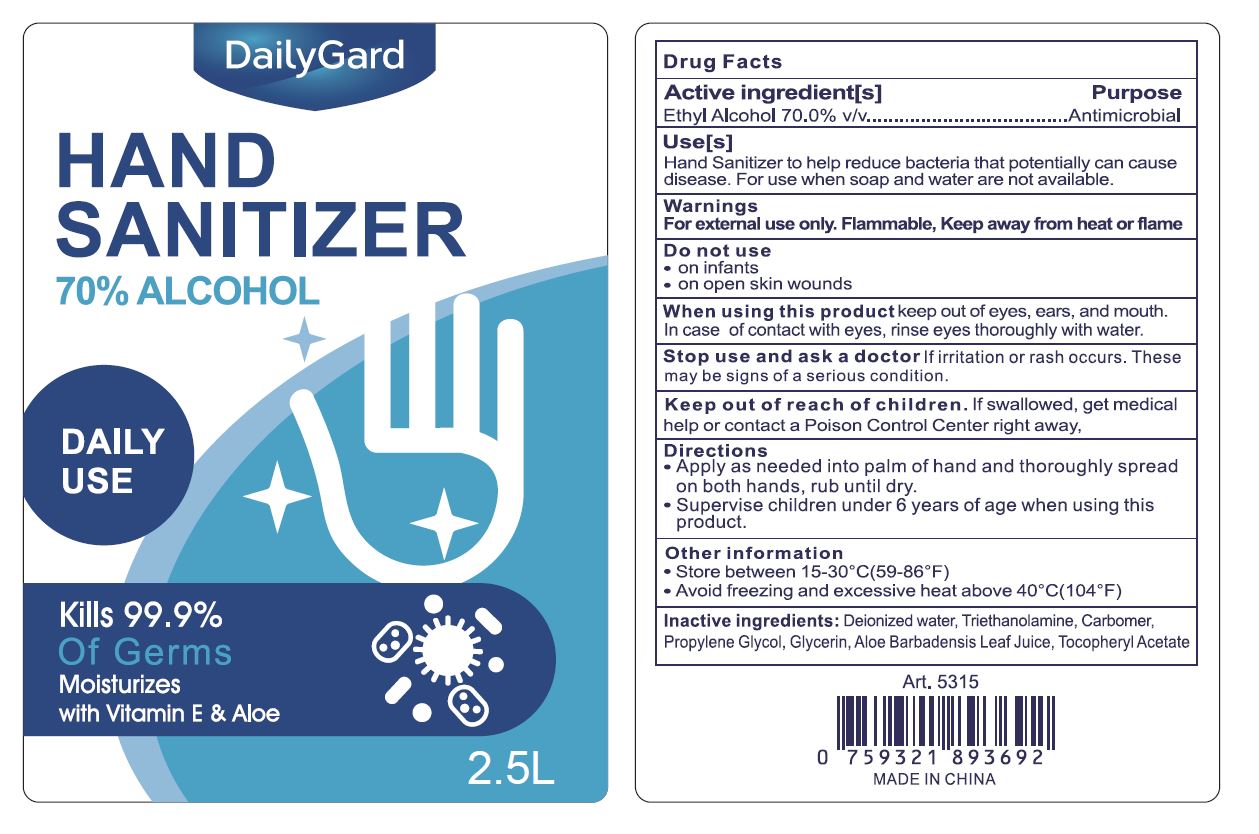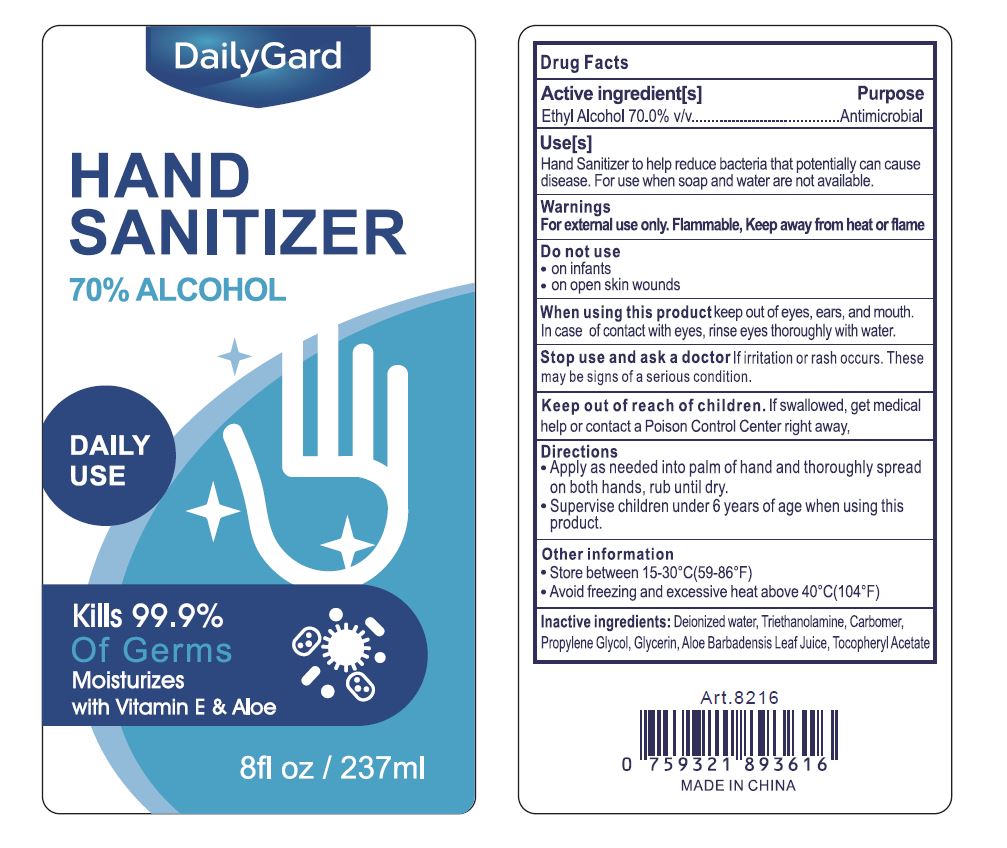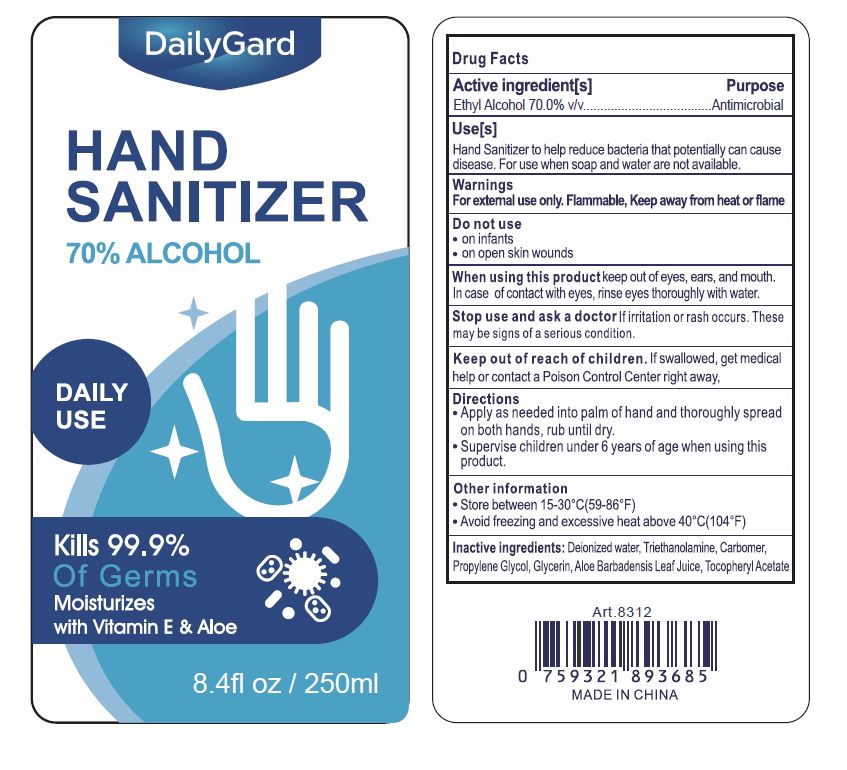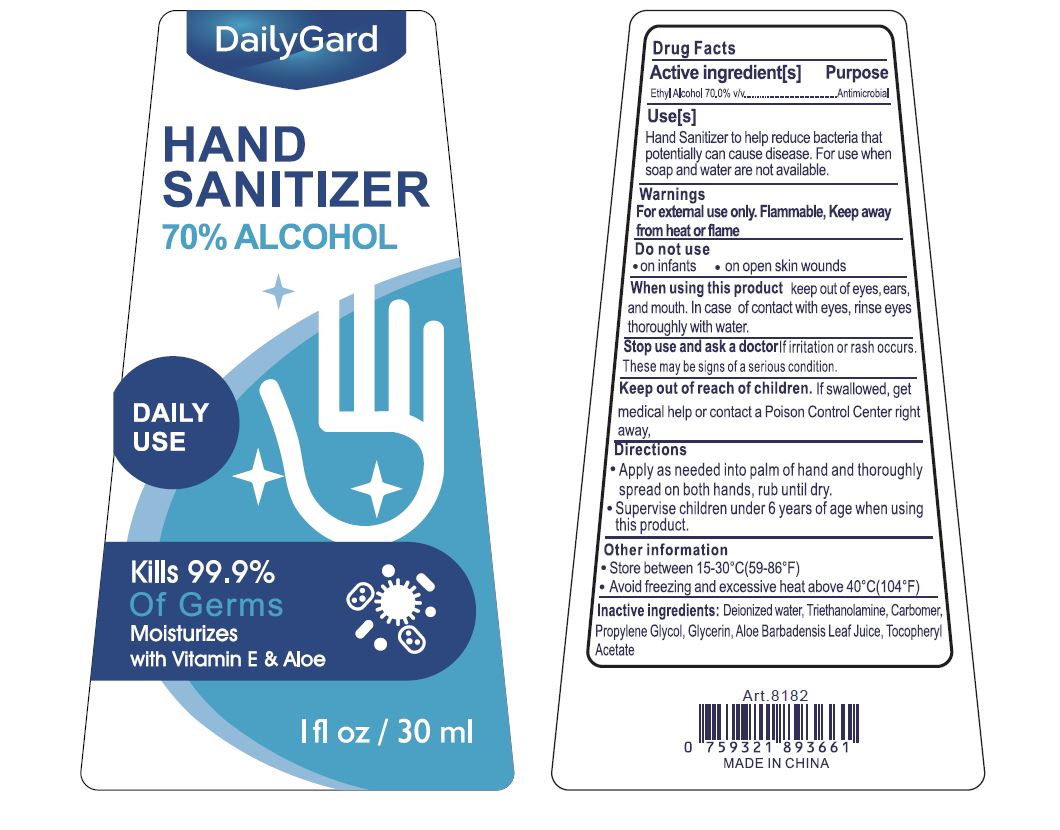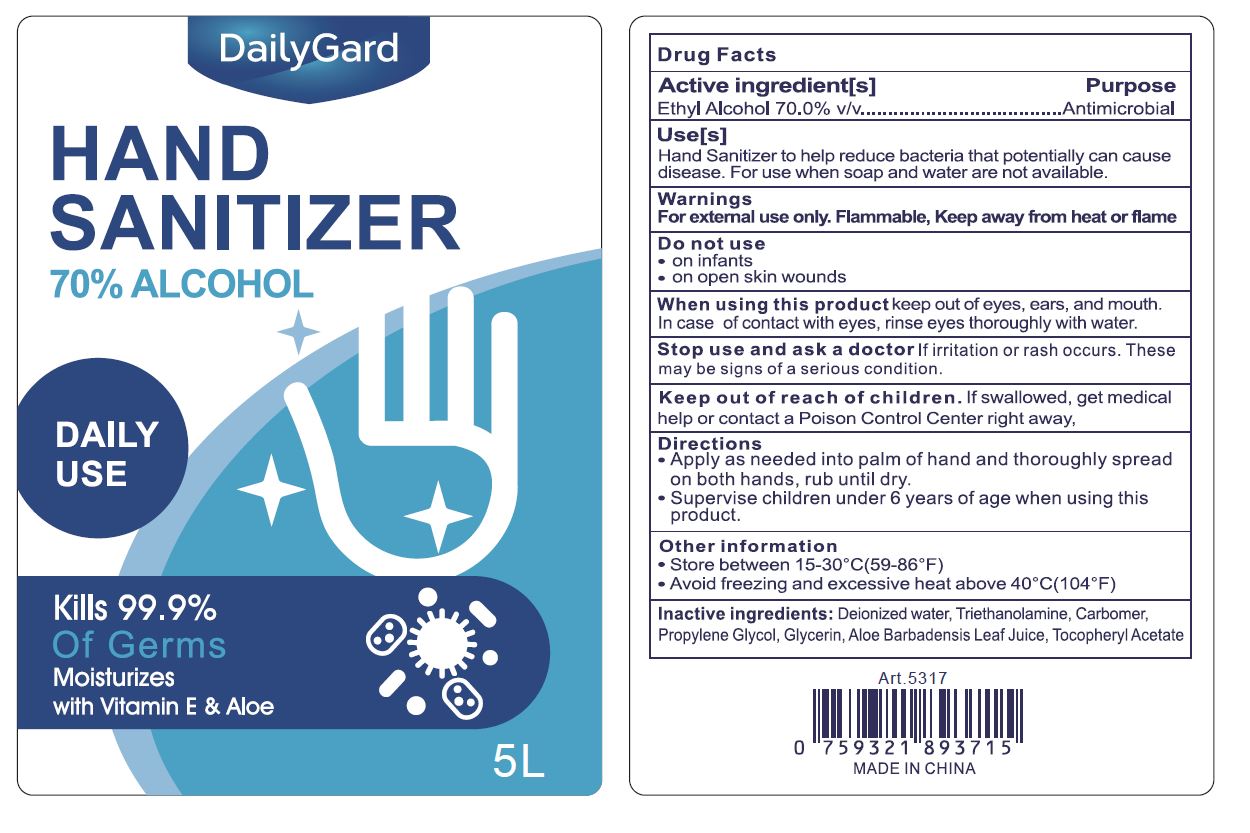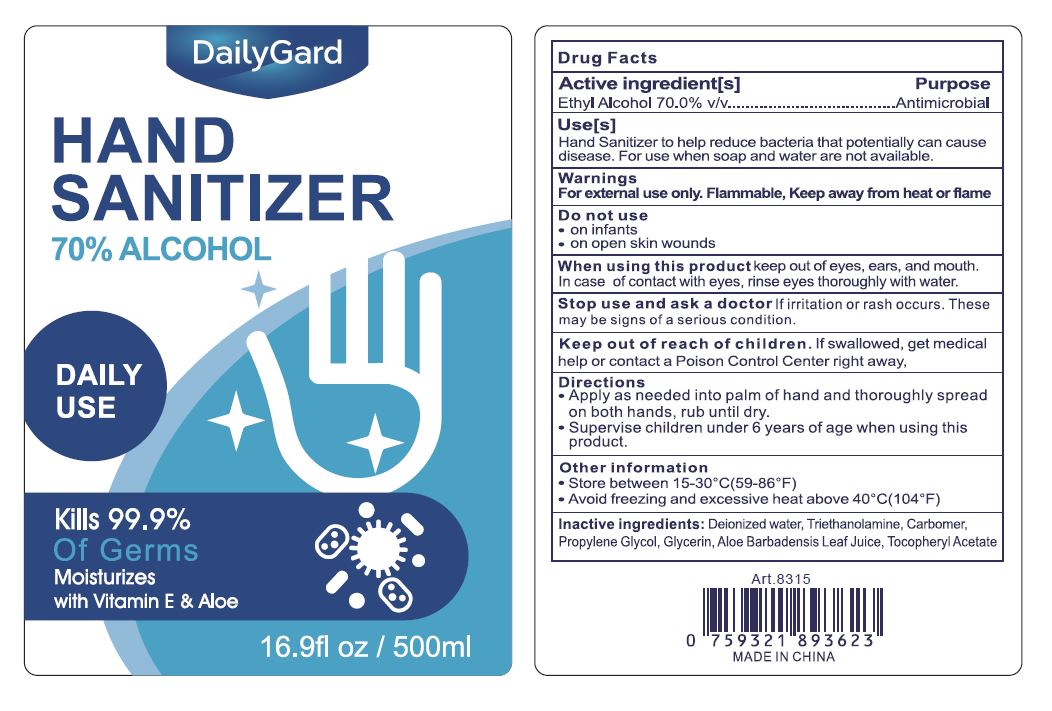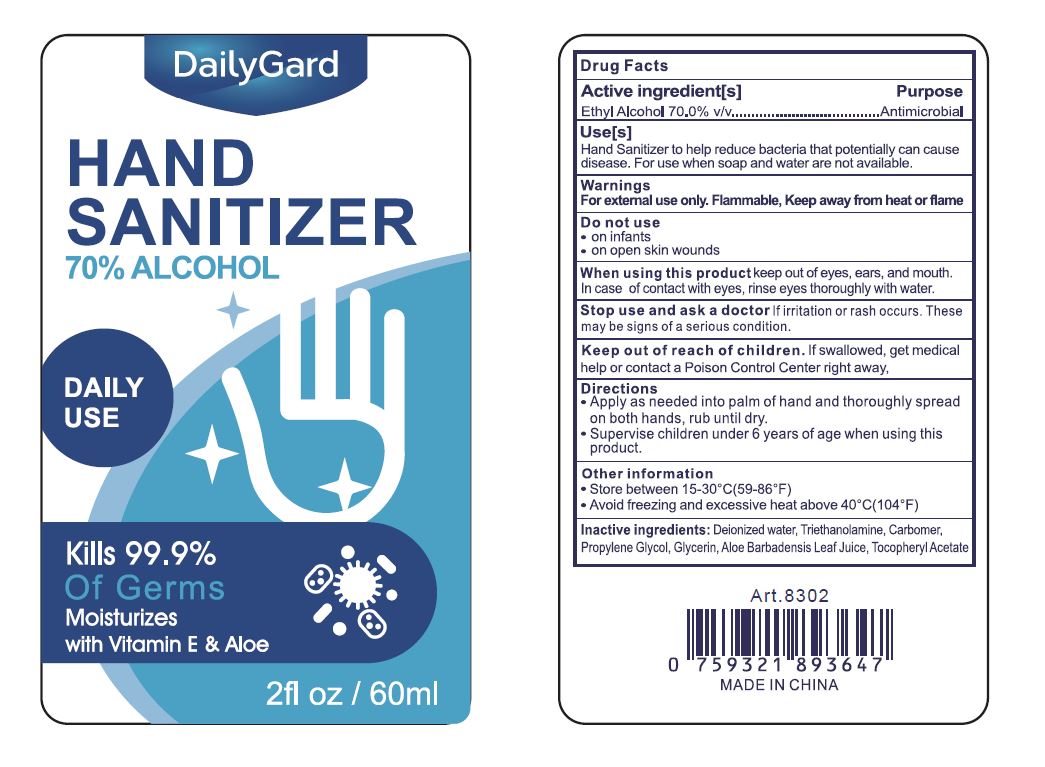 DRUG LABEL: DailyGard Hand Sanitizer
NDC: 75749-015 | Form: LIQUID
Manufacturer: Ningbo Pretty Tourism Manufacturer Co. Ltd.
Category: otc | Type: HUMAN OTC DRUG LABEL
Date: 20200511

ACTIVE INGREDIENTS: ALCOHOL 70 L/100 L
INACTIVE INGREDIENTS: GLYCERIN; WATER; ALOE VERA LEAF; ALPHA-TOCOPHEROL ACETATE; CARBOMER HOMOPOLYMER, UNSPECIFIED TYPE

DailyGard Hand Sanitizer (PE bottle w/ pump)

Active Ingredient(s)

Ethyl Alcohol 70% Purpose: Antimicrobial

Purpose

Antimicrobial

Uses

Use(s)

Hand Sanitizer to help reduce bacteria that potentially can cause disease. For use when soap and water are not available.

Warnings

For external use only. Flammable, Keep away from heat or flame

Do not use

- on infants
- on open skin wounds

When using this product

- Keep out of eyes, ears, and mouth
- In case of contact with eyes, rinse eyes thoroughly with water

- Stop use and ask a doctor if irritation or rash occurs. These may be signs of a serious conditions.

Keep out of reach of children. If swallowed, get medical help or contact a Poison Control Center right away.

Directions

- Apply as needed into palm of hand and thoroughly spread on both hands, rub unitl dry.
- Supervise children under 6 years of age when using this product

Other information

- Store between 15-30 (59-86 F)
- Avoid freezing and excessive heat above 40 C(104 F)

Inactive ingredients

Deionized water, Triethanolamine, Carbomer, Propylene Glycol, Glycerin, Aloe Barbadensis Leaf Juice, Tocopheryl Acetate